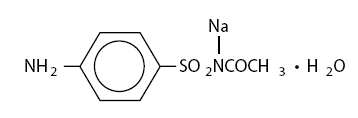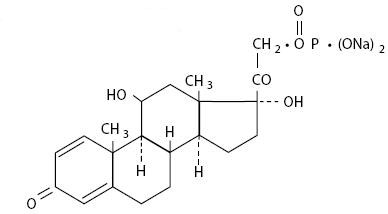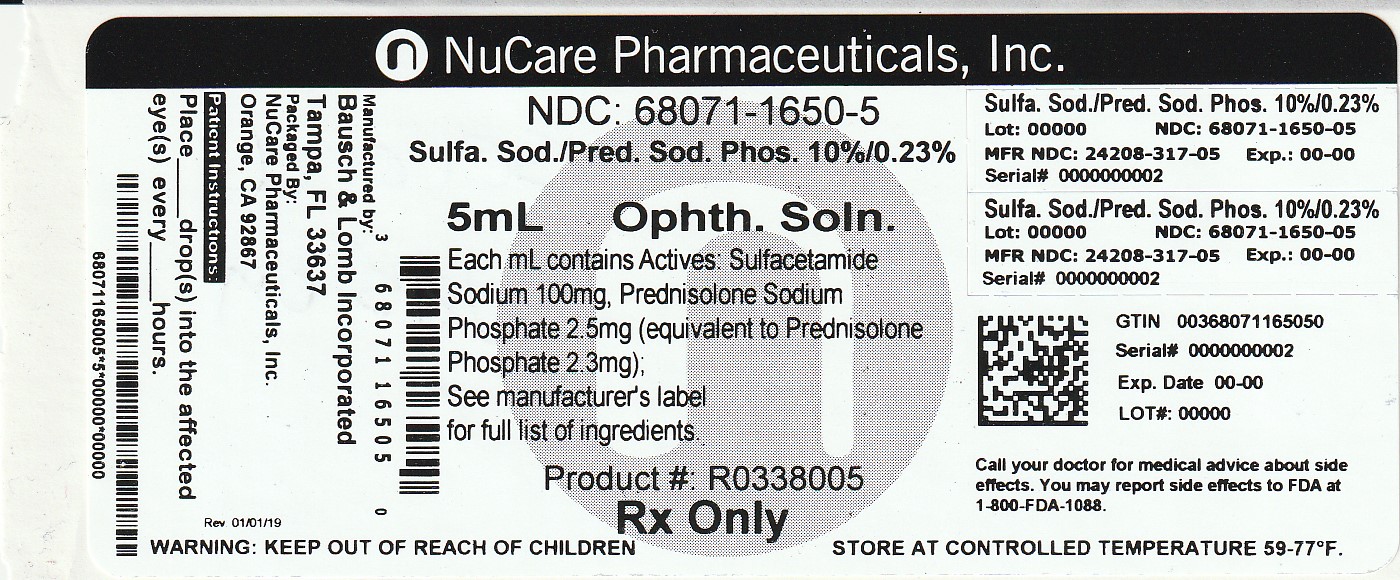 DRUG LABEL: Sulfacetamide Sodium and Prednisolone Sodium Phosphate
NDC: 68071-1650 | Form: SOLUTION/ DROPS
Manufacturer: NuCare Pharmaceuticals,Inc.
Category: prescription | Type: HUMAN PRESCRIPTION DRUG LABEL
Date: 20240715

ACTIVE INGREDIENTS: SULFACETAMIDE SODIUM 100 mg/1 mL; PREDNISOLONE SODIUM PHOSPHATE 2.3 mg/1 mL
INACTIVE INGREDIENTS: POLOXAMER 407; BORIC ACID; EDETATE DISODIUM; WATER; HYDROCHLORIC ACID; SODIUM HYDROXIDE; THIMEROSAL

Sulfacetamide Sodium and Prednisolone Sodium Phosphate
Ophthalmic Solution 10%/0.23%
(prednisolone phosphate) (Sterile)

Rx only

DESCRIPTION

Sulfacetamide Sodium and Prednisolone Sodium Phosphate Ophthalmic Solution is a sterile topical ophthalmic solution combining an anti-infective and an adrenocortical steroid.

Each mL contains: ACTIVES: Sulfacetamide Sodium 100 mg, Prednisolone Sodium Phosphate 2.5 mg (equivalent to Prednisolone Phosphate 2.3 mg); INACTIVES: Poloxamer 407, Boric Acid, Edetate Disodium, Purified Water. Hydrochloric Acid and/or Sodium Hydroxide may be added to adjust pH (6.5-7.5). PRESERVATIVE ADDED: Thimerosal 0.01%.

The chemical name for sulfacetamide sodium is N-sulfanilylacetamide monosodium salt monohydrate.

The chemical name for prednisolone sodium phosphate is 11β, 17, 21-trihydroxypregna-1, 4-diene-3,20-dione, 21-(disodium phosphate).

They have the following structural formulas:

Sulfacetamide Sodium

C8H9N2NaO3S•H2O Mol. Wt. 254.24

Prednisolone Sodium Phosphate

C21H27Na2O8P Mol. Wt. 484.39

CLINICAL PHARMACOLOGY

Corticosteroids suppress the inflammatory response to a variety of agents and they probably delay or slow healing. Since corticosteroids may inhibit the body's defense mechanism against infection, a concomitant antimicrobial drug may be used when this inhibition is considered to be clinically significant in a particular case.

When a decision to administer both a corticosteroid and an antimicrobial is made, the administration of such drugs in combination has the advantage of greater patient compliance and convenience, with the added assurance that the appropriate dosage of both drugs is administered, plus assured compatibility of ingredients when both types of drugs are in the same formulation and, particularly, that the correct amount of drug is delivered and retained.

The relative potency of a corticosteroid depends on the molecular structure, concentration, and release from the vehicle.

Microbiology

Sulfacetamide sodium exerts a bacteriostatic effect against susceptible bacteria by restricting the synthesis of folic acid required for growth through competition with p-aminobenzoic acid.

Some strains of bacteria may be resistant to sulfacetamide or resistant strains may emerge in vivo.

The anti-infective component in Sulfacetamide Sodium and Prednisolone Sodium Phosphate Ophthalmic Solution is included to provide action against specific organisms susceptible to it. Sulfacetamide sodium is active in vitro against susceptible strains of the following microorganisms: Escherichia coli, Staphylococcus aureus, Streptococcus (viridans group) , Haemophilus influenzae, Klebsiella species and Enterobacter species. The product does not provide adequate coverage against: Neisseria species, Pseudomonas species, Serratia marcescens (see INDICATIONS AND USAGE).

INDICATIONS AND USAGE

Sulfacetamide Sodium and Prednisolone Sodium Phosphate Ophthalmic Solution is indicated for corticosteroid-responsive inflammatory ocular conditions for which a corticosteroid is indicated and where superficial bacterial ocular infection or a risk of bacterial ocular infection exists.

Ocular corticosteroids are indicated in inflammatory conditions of the palpebral and bulbar conjunctiva, cornea, and anterior segment of the globe where the inherent risk of corticosteroid use in certain infective conjunctivitides is accepted to obtain diminution in edema and inflammation. They are also indicated in chronic anterior uveitis and corneal injury from chemical, radiation, or thermal burns or penetration of foreign bodies.

The use of a combination drug with an anti-infective component is indicated where the risk of superficial ocular infection is high or where there is an expectation that potentially dangerous numbers of bacteria will be present in the eye.

The particular anti-infective drug in this product is active against the following common bacterial eye pathogens: Escherichia coli, Staphylococcus aureus, Streptococcus pneumoniae, Streptococcus (viridans group), Haemophilus influenzae, Klebsiella species, and Enterobacter species.

This product does not provide adequate coverage against: Neisseria species, Serratia marcescens.

A significant percentage of staphylococcal isolates are completely resistant to sulfa drugs.

CONTRAINDICATIONS

Sulfacetamide Sodium and Prednisolone Sodium Phosphate Ophthalmic Solution is contraindicated in most viral diseases of the cornea and conjunctiva including epithelial herpes simplex keratitis (dendritic keratitis), vaccinia, and varicella, and also in mycobacterial infection of the eye and fungal diseases of ocular structures. This product is also contraindicated in individuals with known or suspected hypersensitivity to any of the ingredients of this preparation, to other sulfonamides, or to other corticosteroids. (Hypersensitivity to the antimicrobial components occurs at a higher rate than for other components).

WARNINGS

NOT FOR INJECTION INTO THE EYE.

Prolonged use of corticosteroids may result in ocular hypertension/glaucoma with damage to the optic nerve, defects in visual acuity and fields of vision, and in posterior subcapsular cataract formation.

Acute anterior uveitis may occur in susceptible individuals, primarily Blacks.

Prolonged use of Sulfacetamide Sodium and Prednisolone Sodium Phosphate Ophthalmic Solution may suppress the host response and thus increase the hazard of secondary ocular infections. In those diseases causing thinning of the cornea or sclera, perforations have been known to occur with the use of topical corticosteroids. In acute purulent conditions of the eye, corticosteroids may mask infection or enhance existing infection.

If this product is used for 10 days or longer, intraocular pressure should be routinely monitored even though it may be difficult in children and uncooperative patients. Corticosteroids should be used with caution in the presence of glaucoma. Intraocular pressure should be checked frequently.

The use of corticosteroids after cataract surgery may delay healing and increase the incidence of filtering blebs.

The use of ocular corticosteroids may prolong the course and may exacerbate the severity of many viral infections of the eye (including herpes simplex). Employment of corticosteroid medication in the treatment of herpes simplex requires great caution.

A significant percentage of staphylococcal isolates are completely resistant to sulfonamides.

Topical corticosteroids are not effective in mustard gas keratitis and Sjögren's keratoconjunctivitis.

Fatalities have occurred, although rarely, due to severe reactions to sulfonamides including Stevens-Johnson syndrome, toxic epidermal necrolysis, fulminant hepatic necrosis, agranulocytosis, aplastic anemia, and other blood dyscrasias. Sensitizations may recur when a sulfonamide is readministered irrespective of the route of administration. If signs of hypersensitivity or other serious reactions occur, discontinue use of this preparation. Cross-sensitivity among corticosteroids have been demonstrated (see ADVERSE REACTIONS).

Do not administer this product to patients who are sensitive/allergic to thimerosal or any other mercury containing ingredient.

PRECAUTIONS

General

The initial prescription and renewal of the medication order beyond 20 mL of Sulfacetamide Sodium and Prednisolone Sodium Phosphate Ophthalmic Solution should be made by a physician only after examination of the patient with the aid of magnification such as slit-lamp biomicroscopy and, where appropriate, fluorescein staining. If signs and symptoms fail to improve after two days, the patient should return to the office for further evaluation.

The possibility of fungal infections of the cornea should be considered after prolonged corticosteroid dosing. Fungal cultures should be taken when appropriate.

The p-aminobenzoic acid present in purulent exudates competes with sulfonamides and can reduce their effectiveness.

Sulfonamide solutions darken on prolonged standing and exposure to heat and light. Do not use if solution has darkened. Yellowing does not affect activity.

Information For Patients

If inflammation or pain persists longer than 48 hours or becomes aggravated, the patient should be advised to discontinue use of the medication and consult a physician.

This product is sterile when packaged. To prevent contamination, care should be taken to avoid touching dropper tip to eyelids or to any other surface. The use of this dispenser by more than one person may spread infection. Keep bottle tightly closed when not in use. Protect from light. Sulfonamide solutions darken on prolonged standing and exposure to heat and light. Do not use if solution has darkened. Yellowing does not affect activity. Keep out of the reach of children.

Laboratory Tests

Eyelid cultures and tests to determine the susceptibility of organisms to sulfacetamide may be indicated if signs and symptoms persist or recur in spite of the recommended course of treatment with Sulfacetamide Sodium and Prednisolone Sodium Phosphate Ophthalmic Solution.

Drug Interactions

Sulfacetamide Sodium and Prednisolone Sodium Phosphate Ophthalmic Solution is incompatible with silver preparations. Local anesthetics related to p-aminobenzoic acid may antagonize the action of the sulfonamides.

Carcinogenesis, Mutagenesis, and Impairment of Fertility

Prednisolone has been reported to be noncarcinogenic. Long-term animal studies for carcinogenic potential have not been performed with prednisolone or sulfacetamide.

One author detected chromosomal nondisjunction in the yeast Saccharomyces cerevisiae following application of sulfacetamide sodium. The significance of this finding to the topical ophthalmic use of sulfacetamide sodium in the human is unknown.

Mutagenic studies with prednisolone have been negative. Studies on reproduction and fertility have not been performed with sulfacetamide. A long-term chronic toxicity study in dogs showed that high oral doses of prednisolone prevented estrus. A decrease in fertility was seen in male and female rats that were mated following oral dosing with another glucocorticosteroid.

Pregnancy

Teratogenic Effects

Prednisolone has been shown to be teratogenic in rabbits, hamsters, and mice. In mice, prednisolone has been shown to be teratogenic when given in doses 1 to 10 times the human ocular dose. Dexamethasone, hydrocortisone and prednisolone were ocularly applied to both eyes of pregnant mice five times per day on days 10 through 13 of gestation. A significant increase in the incidence of cleft palate was observed in the fetuses of the treated mice. There are no adequate, well-controlled studies in pregnant women dosed with corticosteroids.

Kernicterus may be precipitated in infants by sulfonamides given systemically during the third trimester of pregnancy. It is not known whether sulfacetamide sodium can cause fetal harm when administered to a pregnant woman or whether it can affect reproductive capacity.

Sulfacetamide Sodium and Prednisolone Sodium Phosphate Ophthalmic Solution should be used during pregnancy only if the potential benefit justifies the potential risk to the fetus.

Nursing Mothers

It is not known whether topical administration of corticosteroids could result in sufficient systemic absorption to produce detectable quantities in human milk. Systemically administered corticosteroids appear in human milk and could suppress growth, interfere with endogenous corticosteroid production, or cause other untoward effects. Systemically administered sulfonamides are capable of producing kernicterus in infants of lactating women. Because of the potential for serious adverse reactions in nursing infants from sulfacetamide sodium and prednisolone sodium phosphate ophthalmic solution, a decision should be made whether to discontinue nursing or to discontinue the medication.

Pediatric Use

Safety and effectiveness in pediatric patients below the age of 6 years have not been established.

ADVERSE REACTIONS

Adverse reactions have occurred with corticosteroid/anti-infective combination drugs which can be attributed to the corticosteroid component, the anti-infective component, or the combination. Exact incidence figures are not available since no denominator of treated patients is available.

Reactions occurring most often from the presence of the anti-infective ingredient are allergic sensitizations. Fatalities have occurred, although rarely, due to severe reactions to sulfonamides including Stevens-Johnson syndrome, toxic epidermal necrolysis, fulminant hepatic necrosis, agranulocytosis, aplastic anemia, and other blood dyscrasias (see WARNINGS).

Sulfacetamide sodium may cause local irritation.

The reactions due to the corticosteroid component in decreasing order of frequency are: elevation of intraocular pressure (IOP) with possible development of glaucoma, and infrequent optic nerve damage; posterior subcapsular cataract formation; and delayed wound healing.

Although systemic effects are extremely uncommon, there have been rare occurrences of systemic hypercorticoidism after use of topical corticosteroids.

Corticosteroid-containing preparations can also cause acute anterior uveitis or perforation of the globe. Mydriasis, loss of accommodation and ptosis have occasionally been reported following local use of corticosteroids.

Secondary Infection

The development of secondary infection has occurred after use of combinations containing corticosteroids and antimicrobials. Fungal and viral infections of the cornea are particularly prone to develop coincidentally with long-term applications of corticosteroid. The possibility of fungal invasion must be considered in any persistent corneal ulceration where corticosteroid treatment has been used.

Secondary bacterial ocular infection following suppression of host responses also occurs.

To report SUSPECTED ADVERSE REACTIONS, contact Bausch + Lomb, a division of Valeant Pharmaceuticals North America LLC, at 1-800-321-4576 or FDA at 1-800-FDA-1088 or www.fda.gov/medwatch.

DOSAGE AND ADMINISTRATION

Instill two drops of Sulfacetamide Sodium and Prednisolone Sodium Phosphate Ophthalmic Solution topically in the eye(s) every four hours. Not more than 20 mL should be prescribed initially. If signs and symptoms fail to improve after two days, patients should be re-evaluated (see PRECAUTIONS).

Care should be taken not to discontinue therapy prematurely. In chronic conditions, withdrawal of treatment should be carried out by gradually decreasing the frequency of application.

FOR OPHTHALMIC USE ONLY

HOW SUPPLIED

Sulfacetamide Sodium and Prednisolone Sodium Phosphate Ophthalmic Solution 10%/0.23% (prednisolone phosphate) is supplied in a plastic bottle with a white cap and controlled drop tip in the following sizes:

5 mL bottle – NDC68071-1650-5

DO NOT USE IF IMPRINTED NECKBAND IS NOT INTACT.

Storage:

Store between 15°–25°C (59°–77°F). KEEP FROM FREEZING. PROTECT FROM LIGHT. KEEP TIGHTLY CLOSED. Sulfonamide solutions darken on prolonged standing and exposure to heat and light. Do not use if solution has darkened. Yellowing does not affect activity.

KEEP OUT OF REACH OF CHILDREN.

Revised: July 2016

Bausch + Lomb, a division of Valeant Pharmaceuticals North America LLC
Bridgewater, NJ 08807 USA
©Bausch & Lomb Incorporated

9118004 (Folded)
9118104 (Flat)